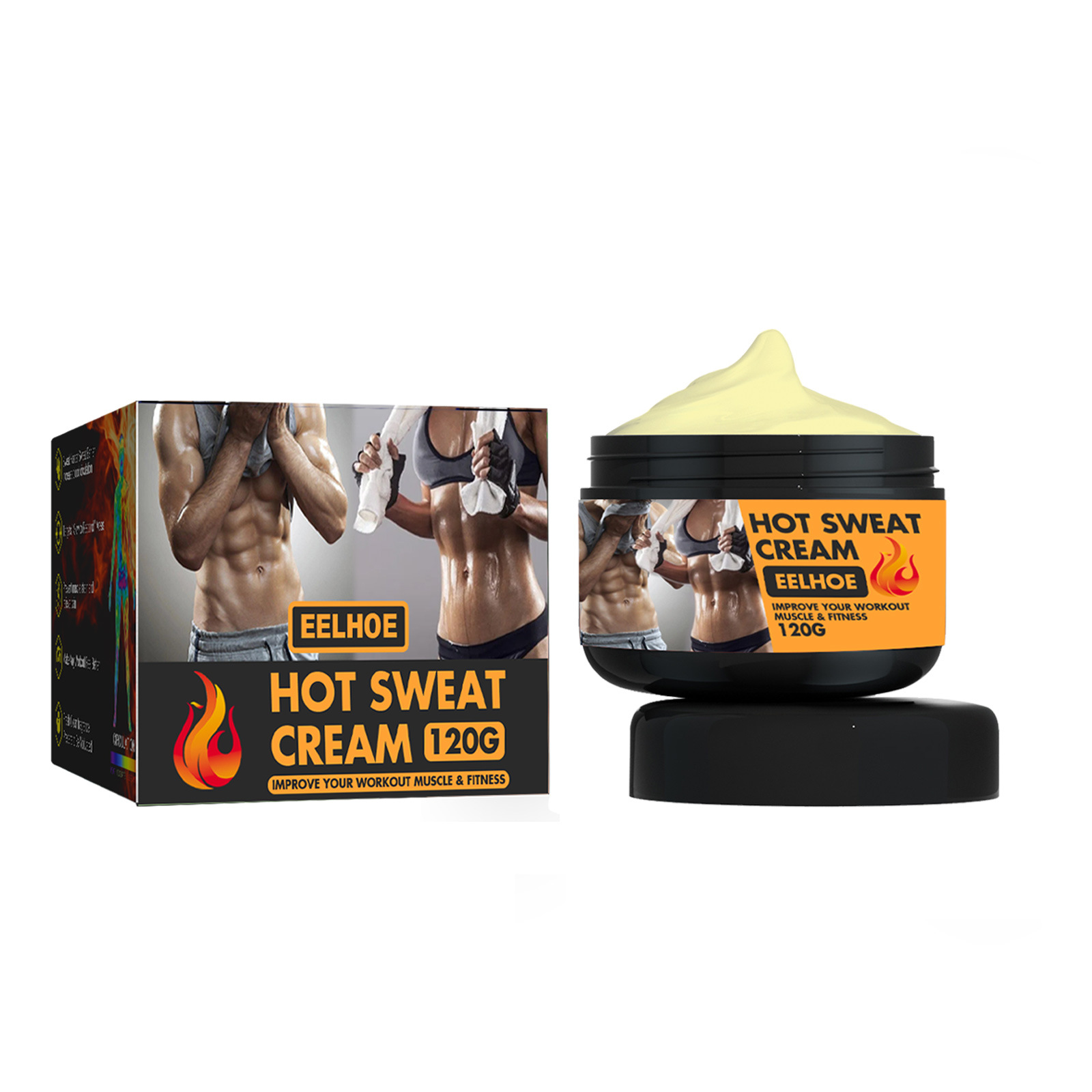 DRUG LABEL: Hot Sweat Cream
NDC: 83675-020 | Form: CREAM
Manufacturer: Guangzhou Hanhai Trading Co., Ltd
Category: otc | Type: HUMAN OTC DRUG LABEL
Date: 20231007

ACTIVE INGREDIENTS: PROPYLENE GLYCOL 19 g/100 g
INACTIVE INGREDIENTS: CETYL ALCOHOL; WATER

Active Ingredient

Propylene Glycol 19.0%

Purpose

Improve Your Workout&Muscle&Fitness

Use

Prevents slowingdown the formationof lactic acid
It acceleratessweating, reducesheat, and improvedblood circulation
Extend exercisetime and shortenrecovery time

Warnings

For external use only. Do not take it internally.

Keep Out Of Reach Of Children
Sensitive Skin

Do not use

Product shall not be eat

When Using

1.After cleaning the abdomen .take appropriate gel evenlyon the abdomen and waist
2.wth the palm loop massage the abdomenback and forth and up and dowfor 5-10minutes until the productis completer absorbed bv the skin
3.This process skinfeeling a slight fever
4.Recommend with regular habltsand a healthy diet in order toachieve better useof results

Stop Use

In case of adverse reactions, please stop using this product.If the symptoms.

Ask Doctor

ask doctor in case of Sensitive Skin

Keep Oot Of Reach Of Children

Keep Out Of Reach Of Children

Directions

1.After cleaning the abdomen .take appropriate gel evenlyon the abdomen and waist
2.wth the palm loop massage the abdomenback and forth and up and dowfor 5-10minutes until the productis completer absorbed bv the skin
3.This process skinfeeling a slight fever
4.Recommend with regular habltsand a healthy diet in order toachieve better useof results

Other information

Store the product in a cool, dry and well-ventilated place

Avoid direct sunlight

Inactive ingredients

Cetyl Alcohol
Water